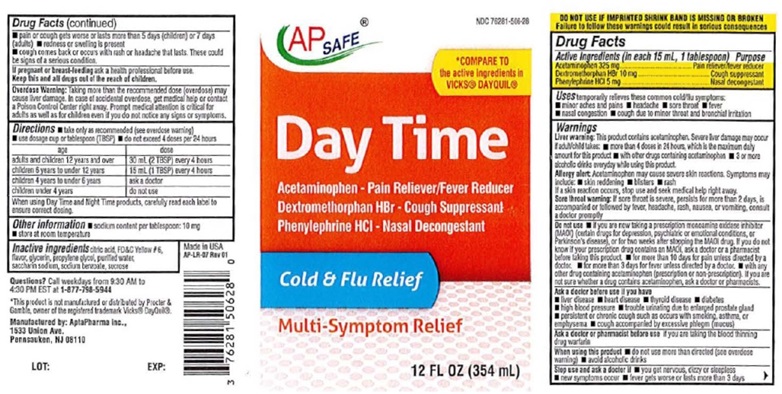 DRUG LABEL: Day-Time Cold/Flu Relief
NDC: 76281-506 | Form: LIQUID
Manufacturer: AptaPharma Inc.
Category: otc | Type: HUMAN OTC DRUG LABEL
Date: 20231211

ACTIVE INGREDIENTS: Acetaminophen 325 mg/15 mL; DEXTROMETHORPHAN HYDROBROMIDE 10 mg/15 mL; PHENYLEPHRINE HYDROCHLORIDE 5 mg/15 mL
INACTIVE INGREDIENTS: CITRIC ACID MONOHYDRATE; FD&C YELLOW NO. 6; GLYCERIN; PROPYLENE GLYCOL; WATER; SACCHARIN SODIUM; SODIUM BENZOATE; SUCROSE

Day Time Cold & Flu Relief

Drug Facts

Active Ingredients (in each 15 mL, 1 tablespoon)

Acetaminophen 325 mg
Dextromethorphan HBr 10 mg
Phenylephrine HCI 5 mg

Purpose

Pain reliever/fever reducer
Cough suppressant
Nasal decongestant

Uses

temporarily relieves these common cold/flu symptoms:
■ minor aches and pains ■ headache ■ sore throat ■ fever
■ nasal congestion ■ cough due to minor throat and bronchial irritation

Warnings

Liver warning: This product contains acetaminophen. Severe liver damage may occur if adult/child takes: ■ more than
4 doses in 24 hours, which is the maximum daily amount for this product ■ with other drugs containing
acetaminophen ■ 3 or more alcoholic drinks everyday while usina this product.
Allergy alert: Acetaminophen may cause severe skin reactions. Symptoms may include: ■ skin reddening ■ blisters ■ rash
If a skin reaction occurs, stop use and seek medical help right away.
Sore throat warning: If sore throat is severe, persists for more than 2 days, is accompanied or followed by fever, headache, rash, nausea, or vomiting, consult a doctor promptly

Do not use

■ if you are now taking a prescription monoamine oxidase inhibitor (MAOI) (certain drugs for depression, psychiatric or emotional conditions, or Parkinson’s disease), or for two weeks after stopping the MAOI drug. If you do not know if your prescription drug contains an MAOI, ask a doctor or a pharmacist before taking this product. ■ for more than 10 days for pain unless directed by a doctor. ■ for more than 3 days for fever unless directed by a doctor. ■ with any other drug containing acetaminophen (prescription or non-prescription). If you are not sure whether a drug contains acetaminophen, ask a doctor or pharmacists.

Ask a doctor before use if you have

■ liver disease ■ heart disease ■ thyroid disease ■ diabetes
■ high blood pressure ■ trouble urinating due to enlarged prostrate gland
■ persistent or chronic cough such as occurs with smoking, asthma, or
emphysema ■ cough accompanied by excessive phlegm (mucus)

Ask a doctor or pharmacist before use

if you are taking the blood thinning
drug warfarin

When using this product

■ do not use more than directed (see overdose
warning) ■ avoid alcoholic drinks

Stop use and ask a doctor if

■ you get nervous, dizzy or sleepless
■ new symptoms occur
■ fever gets worse or lasts more than 3 days
■ pain or cough gets worse or lasts more than 5 days (children) or 7 days (adults)
■ redness or swelling is present
■ cough comes back or occurs with rash or headache that lasts.
These couldbe signs of a serious condition.

If pregnant or breast-feeding

ask a health professional before use.

KEEP OUT OF REACH OF CHILDREN

Keep this and all drugs out of the reach of children.

Overdose Warning:

Taking more than the recommended dose (overdose) may
cause liver damage. In case of accidental overdose, get medical help or contact
a Poison Control Center right away. Prompt medical attention is critical for adults
as well as for children even if you do not notice any signs or symptoms.

Directions

■ take only as recommended (see overdose warning)
■ use dosage cup or tablespoon (TBSP)
■ do not exceed 4 doses per 24 hours

age dose
adults & children 12 years and over 30 mL (2 TBSP) every 4 hours
children 6 to under 12 years 15 mL (1 TBSP) every 4 hours
children 4 to under 6 years ask a doctor
children under 4 years do not use

When using Day Time and Night Time products, carefully read each label to
ensure correct dosing.

Other information

■ sodium content per tablespoon: 10 mg
■ store at room temperature

Inactive Ingredients

citric acid, FD&C Yellow # 6, Made in USA flavor, glycerin, propylene glycol, purified water,
saccharin sodium, sodium benzoate, sucrose

Questions?

Call weekdays from 9:30 AM to
4:30 PM EST at 1-877-798-5944

Product Package Label - Day Time Cold & Flu Relief

AP SAFE

*COMPARE TO
the active ingredients in
VICKS® DAYQUIL®

Day Time

Acetaminophen – Pain Reliever/Fever Reducer
Dextromethorphan HBr – Cough Suppressant
Phenylephrine HCI – Nasal Decongestant

Cold & Flu Relief

Multi-Symptom Relief

12 FL OZ (354 mL)

*This product is not manufactured or distributed by Procter &
Gamble, owner of the registered trademark Vicks® DayQuil®.

Manufactured by: AptaPharma Inc.,
1533 Union Ave.
Pennsauken, NJ 08110

LOT: EXP:

12 OZ

res